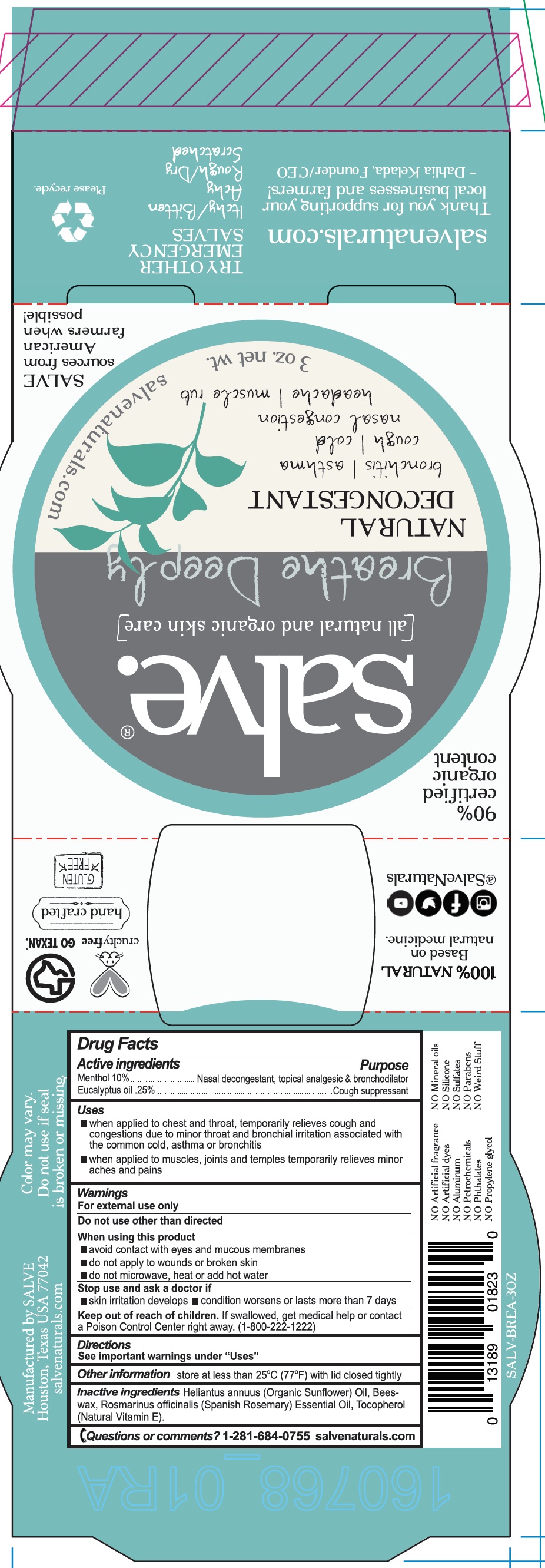 DRUG LABEL: Breathe Deeply
NDC: 71157-0019 | Form: CREAM
Manufacturer: Kelada Creative Group
Category: otc | Type: HUMAN OTC DRUG LABEL
Date: 20181226

ACTIVE INGREDIENTS: MENTHOL 170 g/90 mL
INACTIVE INGREDIENTS: SUNFLOWER OIL; WHITE WAX; .ALPHA.-TOCOPHEROL; ROSEMARY OIL; EUCALYPTUS OIL

Breathe Deeply

ACTIVE INGREDIENT

Menthol 10%

Eucalyptus oil .25%

PURPOSE

- When applied to chest and throat, temporarily relieves cough and congestions due to minor throat and bronchial irritation associated with the common cold, asthma, or bronchitis

DOSAGE AND ADMINISTRATION

- Temporarily relieves itching and discomfort associated with irritation, inflammation, and rashes due to insect bites, stings, poison ivy, oak and sumac

WARNINGS

For external use only

Do not use other than as directed

When using this product

- avoid contact with eyes and mucous membranes
- do not apply to wounds or broken skin
- do not microwave, hear or add hot water

INACTIVE INGREDIENT

Organic sunflower oil, Beeswax, Spanish Rosemary essential oil, Natural Vitamin E

KEEP OUT OF REACH OF CHILDREN

Keep our of reach of children. If swallowed, get medical help or contact a Poison Control Center right away.

INDICATIONS AND USAGE

- When applied to chest and throat, temporarily relieves cough and congestions due to minor throat and bronchial irritation associated with the common cold, asthma, or bronchitis